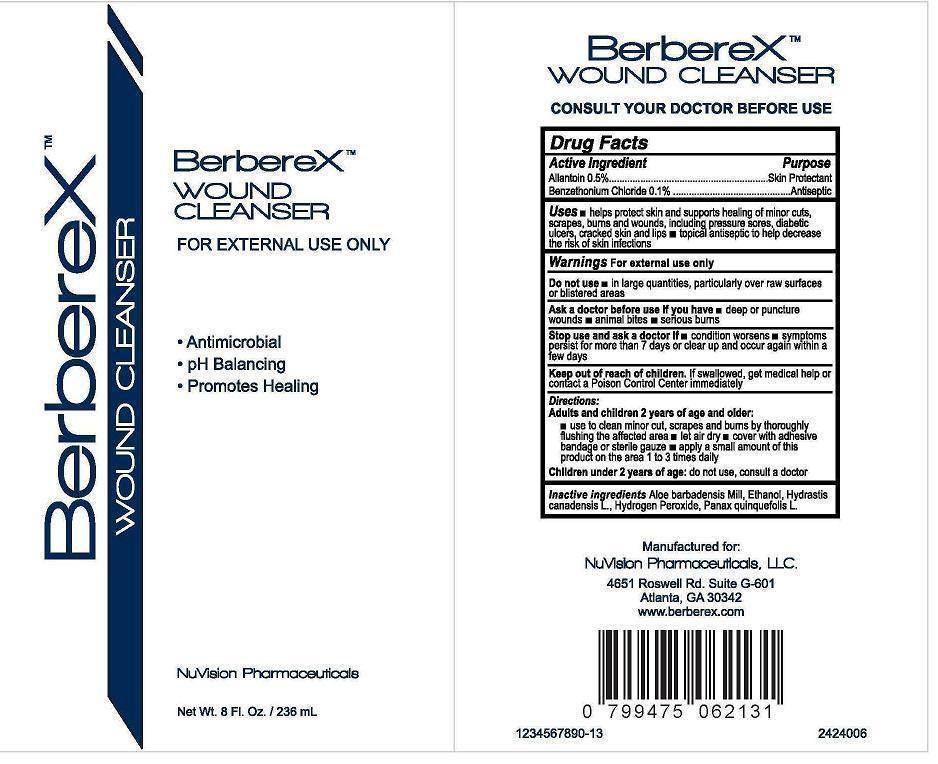 DRUG LABEL: BerbereX Wound Cleanser
NDC: 58133-055 | Form: SOLUTION
Manufacturer: Cosmetic Specialty Labs, Inc.
Category: otc | Type: HUMAN OTC DRUG LABEL
Date: 20140123

ACTIVE INGREDIENTS: ALLANTOIN 5 g/1000 mL; BENZETHONIUM CHLORIDE 1 g/1000 mL
INACTIVE INGREDIENTS: ALOE VERA WHOLE; ALCOHOL; HYDRASTIS CANADENSIS WHOLE; Hydrogen Peroxide; PANAX QUINQUEFOLIUS WHOLE

ACTIVE INGREDIENT

- Allantoin 0.5%
- Benzethonium Chloride 0.1%

PURPOSE

- Skin Protectant
- Antiseptic

KEEP OUT OF REACH OF CHILDREN

If swallowed, get medical help or contact a poison control center immediately.

USES

helps protect skin and supports healing of minor cuts,

scapes, bums and wounds, including pressure sores, diabetic

ulcers, cracked skin and lips. topical antiseptic to help decrease

the risk of skin infections

WARNINGS

for external use only

Do not use

in large quantities, particularly over raw surfaces or blistered areas

Ask a doctor before use if you have

- deep or puncture wounds
- animal bites
- serious bums

Stop use and ask a doctor if

- condition worsens
- symptoms perist for more than 7days or clear up and occur again within a few days

DIRECTIONS

Adults and children 2years of age and older

Use to clean minor cut, scrapes and burns by thoroughly flushing the affected area; let air dry; cover with adhesive bandage or sterile gauze; apply a small amount of this product on the area 1 to 3 times daily

Children under 2years of age

do not use, consult a doctor

INACTIVE INGREDIENTS

Aloe barbadensis Mill, Ethanol, Hydrastis canadensis L., Hydrogen Peroxide, Panax quinquefolis L.